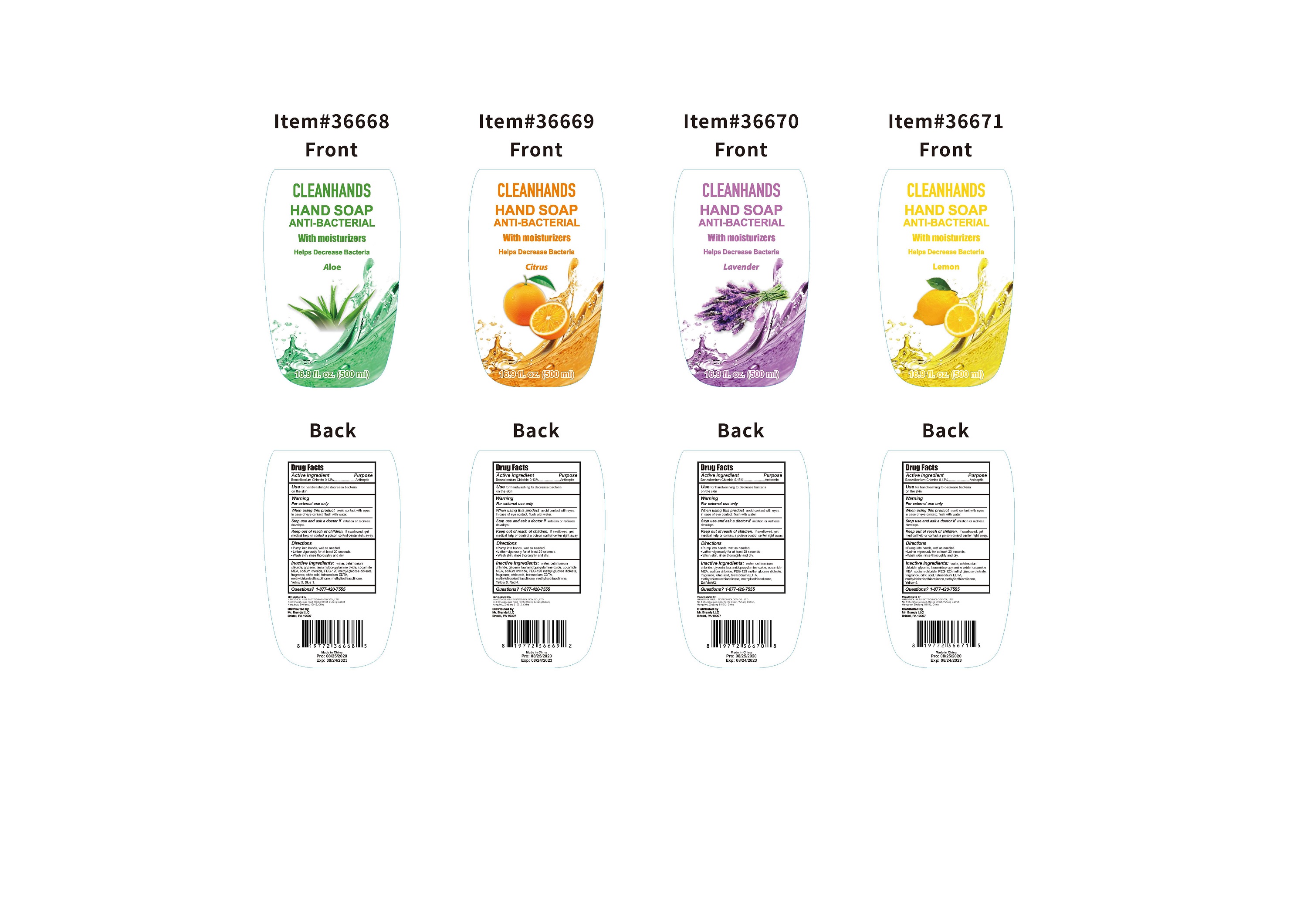 DRUG LABEL: CLEANHANDS
NDC: 73788-108 | Form: SOAP
Manufacturer: Hangzhou Huiji Biotechnology Co., Ltd.
Category: otc | Type: HUMAN OTC DRUG LABEL
Date: 20220224

ACTIVE INGREDIENTS: BENZALKONIUM CHLORIDE 0.13 g/100 g
INACTIVE INGREDIENTS: FD&C RED NO. 4; FD&C YELLOW NO. 5; FD&C BLUE NO. 1; D&C VIOLET NO. 2; PEG-120 METHYL GLUCOSE DIOLEATE; EDETATE SODIUM; WATER; GLYCERIN; CETRIMONIUM CHLORIDE; SODIUM CHLORIDE; LAURAMIDOPROPYLAMINE OXIDE; COCO MONOETHANOLAMIDE; CITRIC ACID MONOHYDRATE; METHYLCHLOROISOTHIAZOLINONE; METHYLISOTHIAZOLINONE

73788-108 Antibacterial liquid hand soap 16.9 fl oz (Benzalkonium chloride 0.13%)

Active Ingredient

Benzalkonium Chloride 0.13%

Purpose

Antibacterial

Use

For hand sanitizing to reduce bacteria
on the skin.

WARNINGS

For external use only
When using this product avoid contact with eyes.
In case of eye contact, flush with water.
Stop use and ask a doctor if irritation or redness
develops.

Keep out of reach of children. If swallowed, get
medical help or contact a poison control center right away.

Directions

●Pump into hands, wet as needed.
●Lather vigorously for at least 15 seconds.
●Wash skin, rinse thoroughly and dry.

Inactive ingredients

water, cetrimonium
chloride, glycerin, lauramidopropylamine oxide, cocamide
MEA, sodium chloride, PEG-120 methyl glucose dioleate,
citric acid, tetrasodium EDTA, methylchloroisothiazolinone,
methylisothiazolinone.yellow5,blue1,red4,violet2